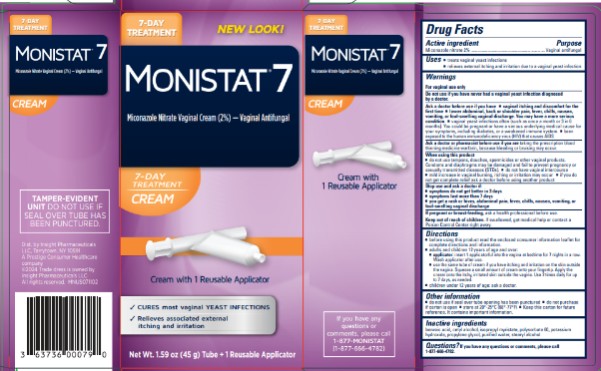 DRUG LABEL: Monistat 7
NDC: 63736-025 | Form: CREAM
Manufacturer: Insight Pharmaceuticals LLC
Category: otc | Type: HUMAN OTC DRUG LABEL
Date: 20251027

ACTIVE INGREDIENTS: Miconazole Nitrate 20 mg/1 g
INACTIVE INGREDIENTS: Benzoic Acid; Cetyl Alcohol; Isopropyl Myristate; Polysorbate 60; Potassium Hydroxide; Propylene Glycol; Water; Stearyl Alcohol

Monistat 7 Cure Itch Relief - ReuseableApps-Cream

Drug Facts

Active ingredients

Miconazole nitrate 2%

Purpose

Vaginal antifungal

Uses

- treats vaginal yeast infections
- relieves external itching and irritation due to a vaginal yeast infection

Warnings

For vaginal use only

Do not use

if you have never had a vaginal yeast infection diagnosed by a doctor.

Ask a doctor before use if you have

- vaginal itching and discomfort for the first time
- lower abdominal, back or shoulder pain, fever, chills, nausea, vomiting, or foul-smelling vaginal discharge. You may have a more serious condition.
- vaginal yeast infections often (such as once a month or 3 in 6 months). You could be pregnant or have a serious underlying medical cause for your symptoms, including diabetes, or a weakened immune system.
- been exposed to the human immunodeficiency virus (HIV) that causes AIDS

Ask a doctor or pharmacist before use if you are

taking the prescription blood thinning medicine warfarin, because bleeding or bruising may occur

When using this product

- do not use tampons, douches, spermicides or other vaginal products. Condoms and diaphragms may be damaged and fail to prevent pregnancy or sexually transmitted diseases (STDs)
- do not have vaginal intercourse
- mild increase in vaginal burning, itching or irritation may occur
- if you do not get complete relief ask a doctor before using another product

Stop use and ask a doctor if:

- symptoms do not get better in 3 days
- symptoms last more than 7 days
- you get a rash or hives, abdominal pain, fever, chills, nausea, committing, or foul-smelling vaginal discharge.

If pregnant or breast-feeding,

ask a health professional before use.

Keep out of reach of children.

If swallowed, get medical help or contact a Poison Control Center right away.

Directions

- before using this product read the enclosed consumer information leaflet for complete directions and information
- adults and children 12 years of age and over:
  ○ applicator: Insert 1 applicatorful into the vagina at bedtime for 7 nights in a row. Wash applicator after use.
  ○ use the same tube of cream if you have itching and irritation on the skin outside the vagina. Squeeze a small amount of cream onto your fingertip. Apply the cream onto the itchy, irritated skin outside the vagina. Use 2 times daily for up to 7 days, as needed.
- children under 12 years of age: ask a doctor.

Other information

- do not use if seal over tube opening has been punctured
- do not purchase if carton is open
- store at 20°-25°C (68°-77°F)
- Keep this carton for future reference. It contains important information.

Inactive ingredients

benzoic acid, cetyl alcohol, isopropyl myristate, polysorbate 60, potassium hydroxide, propylene glycol, purified water, stearyl alcohol.

Questions?

If you have any questions or comments, please call 1-877-666-4782

PRINCIPAL DISPLAY PANEL

MONISTAT® 7
Miconazole Nitrate Vaginal Cream (2%)

Vaginal Antifungal

1 Reusable Applicator

Net Wt. 1.59 oz. (45g) Tube